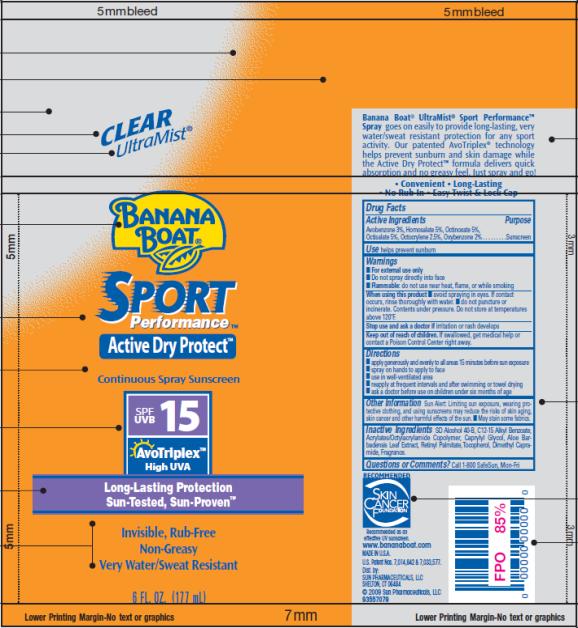 DRUG LABEL: Banana Boat Sport Performance SPF 15
NDC: 17630-2005 | Form: SPRAY
Manufacturer: Accra-Pac, Inc.
Category: otc | Type: HUMAN OTC DRUG LABEL
Date: 20100318

ACTIVE INGREDIENTS: AVOBENZONE 0.03 mL/1 mL; HOMOSALATE 0.05 mL/1 mL; OCTINOXATE 0.05 mL/1 mL; OCTISALATE 0.05 mL/1 mL; OCTOCRYLENE 0.025 mL/1 mL; OXYBENZONE 0.02 mL/1 mL
INACTIVE INGREDIENTS: C12-15 ALKYL BENZOATE; CAPRYLYL GLYCOL; ALOE VERA LEAF; VITAMIN A PALMITATE

Banana Boat Sport Performance SPF 15

Drug Facts

Active ingredients

Avobenzone 0.03mL / 1mL

Homosalate 0.05mL / 1mL

Octinoxate 0.05mL / 1mL

Octisalate 0.05mL / 1mL

Octocrylene 0.025mL / 1mL

Oxybenzone 0.02mL / 1mL

Purpose

Sunscreen

Use

helps prevent sunburn

Warnings

- For external use only
- Do not spray directly into face
- Flammable do not use near heat, flame or while smoking

While using this product

- Avoid spraying in eyes. If contact occurs rinse thoroughly with water.
- Do not puncture or incinerate. Contents under pressure. Do not store at temperatures above 120°F.

Stop use and ask a doctor

if irritation or rash develops

Keep out of reach of children.

If swallowed, get medical help or contact a Poison control center right way.

Directions

- Apply generously and evenly to all areas 15 minutes before sun exposure
- Spray on hands to apply to face
- Use in well-ventilated area
- Reapply at frequent intervals and after swimming or towel drying
- Ask a doctor before use on children under six months of age

Other Information

Sun Alert: Limiting sun exposure, wearing protective clothing, and using sunscreens may reduce the risks of skin aging, skin cancer and other harmful effects of the sun.

- May stain some fabrics.

Inactive Ingredients

SD Alcohol 40-B, C12-15 Alkyl Benzoate, Acrylates/ Octylacrylamide, Copolymer, Caprylyl Glycol, Aloe Barbadensis Leaf Extract, Retinyl Palmitate, Tocopherol, Dimethyl Capramide, Fragrance

Questions or comments?

Call 1-800-SafeSun, Mon-Fri

Distributed by:
Sun Pharmaceuticals, LLC, Shelton, CT 06484
www.bananaboat.com

Manufactured by:
Accra Pac, Inc. (dba KIK Custom Products)

PRINCIPAL DISPLAY PANEL

CLEAR
UltraMist®
Banana
Boat®
SPORT
Performance TM
Active Dry Protect TM
Continuous Spray Sunscreen
SPF/UVB 15
AvoTriplex TM
High UVA
Long-Lasting Protection
Sun-Tested, Sun-Proven TM
Invisible, Rub-Free
Non-Greasy
Very Water/Sweat Resistant
6 FL. OZ. (177 mL)